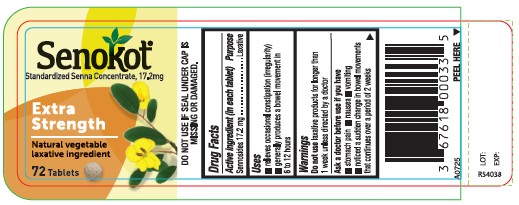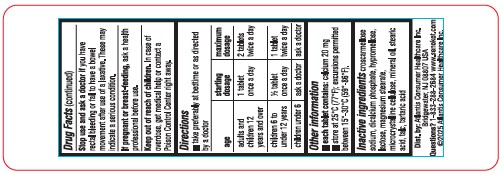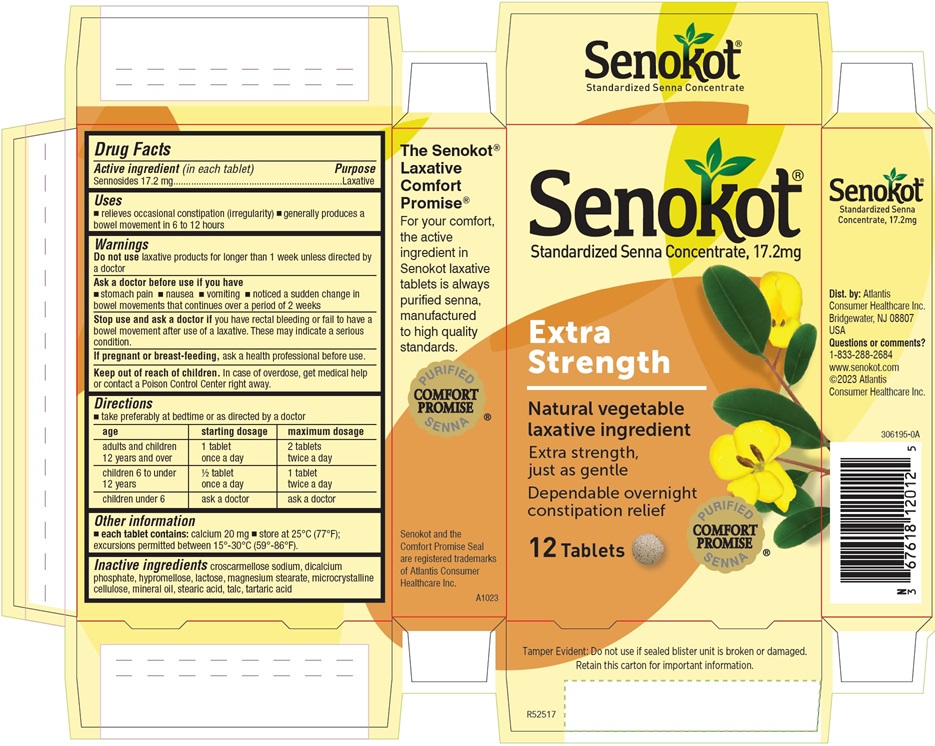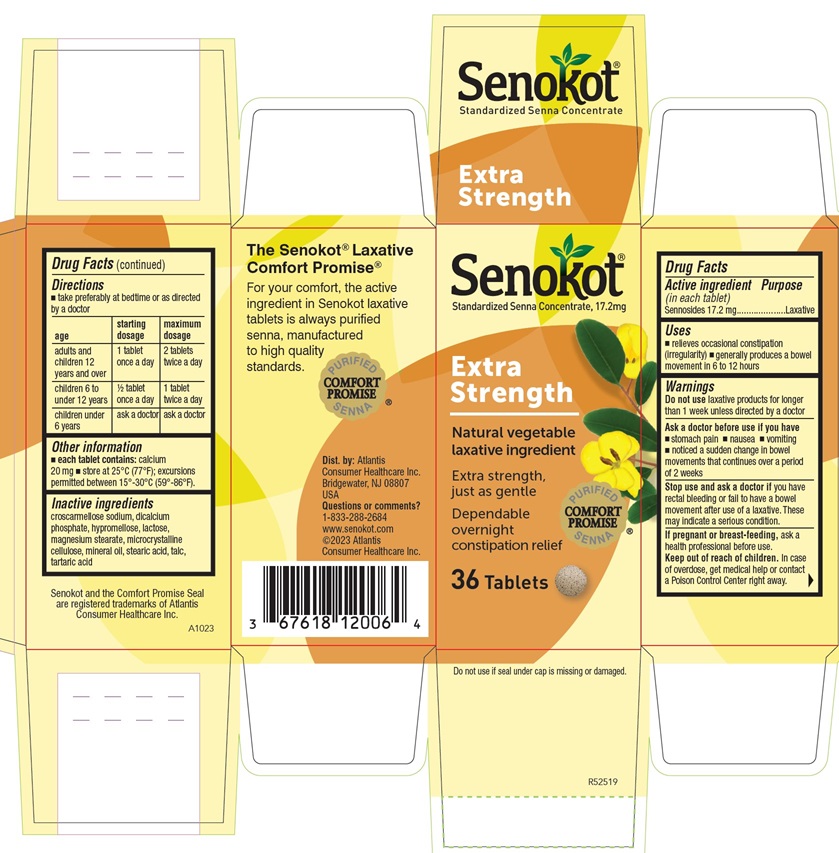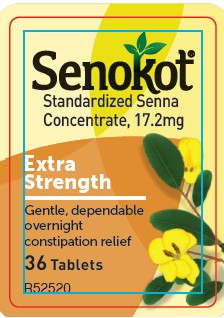 DRUG LABEL: Senokot
NDC: 67618-120 | Form: TABLET, FILM COATED
Manufacturer: Atlantis Consumer Healthcare, Inc.
Category: otc | Type: HUMAN OTC DRUG LABEL
Date: 20250820

ACTIVE INGREDIENTS: SENNOSIDES 17.2 mg/1 1
INACTIVE INGREDIENTS: CROSCARMELLOSE SODIUM; HYPROMELLOSE, UNSPECIFIED; LACTOSE, UNSPECIFIED FORM; MAGNESIUM STEARATE; MICROCRYSTALLINE CELLULOSE; TARTARIC ACID; DIBASIC CALCIUM PHOSPHATE DIHYDRATE; LIGHT MINERAL OIL; TALC; STEARIC ACID

SenokotXTRA
(standardizedsenna concentrate)
Drug Facts

Active ingredient (in each tablet)

Sennosides 17.2 mg

Purpose

Laxative

Uses

- relieves occasional constipation (irregularity)
- generally causes bowel movement in 6-12 hours

Warnings

Do not use laxative products for longer than 1 week unless directed by a doctor

Ask a doctor before use if you have

- stomach pain
- nausea
- vomiting
- noticed a sudden change in bowel movements that continuesover a period of 2 weeks

Stop Use

Stop use and ask a doctor if you have rectal bleeding or fail to have a bowel movement after use of a laxative. These may indicate a serious condition.

Pregnancy or Breast Feeding

If pregnant or breast-feeding, ask a health professional before use.

Keep Out of Reach of Children

In case of overdose, get medical help or contact a Poison Control Center right away.

Directions

- take preferably at bedtime or as directed by a doctor

Dosage Forms & Strengths

age | startingdosage | maximumdosage
adults and children 12 yearsof age and over | 1 tablet once a day | 2 tablets twice aday
children 6 to under 12 years | ½ tablet once a day | 1 tablet twice aday
children under 6 | ask a doctor | ask a doctor

Other Information

- each tablet contains: calcium 20mg
- store at 25°C (75°F); excursions permitted between 15°-30°C (59°-86°F).

Inactive Ingredients

croscarmellose sodium, dicalcium phosphate, hypromellose, lactose, magnesium stearate, microcrystalline cellulose, mineral oil, stearic acid, talc, tartaric acid

PACKAGE LABEL.PRINCIPAL DISPLAY PANEL

Senokot® Extra Strength
36 Tablets Carton

Senokot® Extra Strength
12 Tablets Carton

Senokot® Extra Strength 36 Tablets Label

Senokot®
Standardized Senna Concentrate, 17.2mg
Extra
Strength
Natural vegetable
laxative Ingredient
72 Tablets
DO NOT USE IF SEAL UNDER CAP IS
MISSING OR DAMAGED.
A0725
LOT:
EXP:
R54038
Dist. by: Atlantis Consumer Healthcare Inc.
Bridgewater, NJ 08807 USA
Questions? 1-833-288-2684 www.senokot.com
©2025 Atlantis Consumer Healthcare Inc.